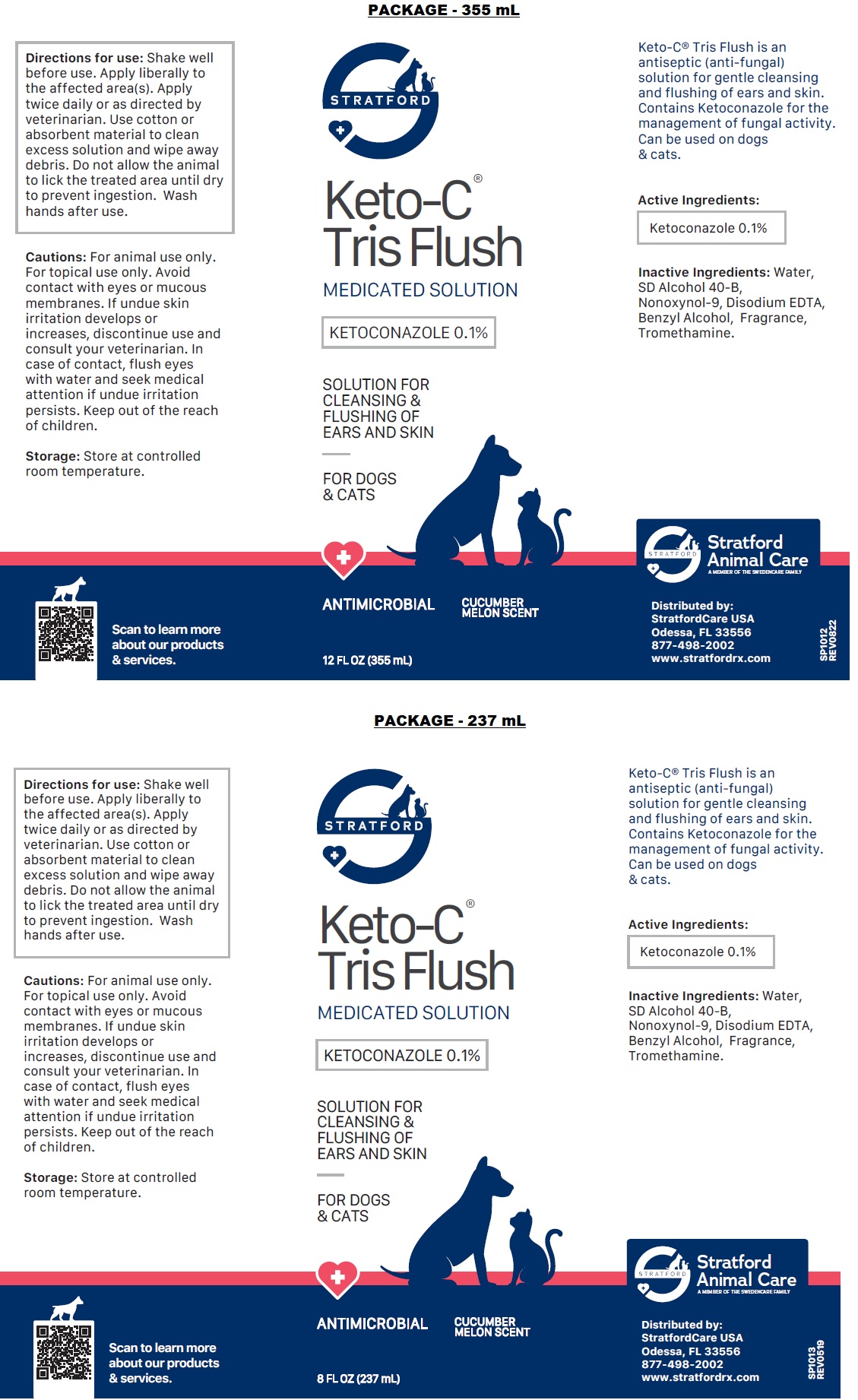 DRUG LABEL: Keto-C-Tris FLUSH
NDC: 86069-111 | Form: SOLUTION
Manufacturer: Stratford Care Usa, Inc.
Category: animal | Type: OTC ANIMAL DRUG LABEL
Date: 20221110

ACTIVE INGREDIENTS: KETOCONAZOLE 0.1 g/100 mL
INACTIVE INGREDIENTS: WATER; ALCOHOL; NONOXYNOL-9; EDETATE DISODIUM ANHYDROUS; BENZYL ALCOHOL; TROMETHAMINE

Keto-C®-Tris FLUSH

Active Ingredients:

Ketoconazole 0.1%

PURPOSE

anti-fungal

INDICATIONS AND USAGE

Keto-C® Tris Flush is an antiseptic (anti-fungal) solution for gentle cleansing and flushing of ears and skin. Contains Ketoconazole for the management of fungal activity. Can be used on dogs & cats.

INACTIVE INGREDIENT

Inactive Ingredients: Water, SD Alcohol 40-B, Nonoxynol-9, Disodium EDTA, Benzyl Alcohol, Fragrance, Tromethamine.

DOSAGE AND ADMINISTRATION

Directions for use: Shake well before use. Apply liberally to the affected area(s). Apply twice daily or as directed by veterinarian. Use cotton or absorbent material to clean excess solution and wipe away debris. Do not allow the animal to lick the treated area until dry to prevent ingestion. Wash hands after use.

PRECAUTIONS

Cautions: For animal use only. For topical use only. Avoid contact with eyes or mucous membranes. If undue skin irritation develops or increases, discontinue use and consult your veterinarian. In case of contact, flush eyes with water and seek medical attention if undue irritation persists. Keep out of the reach of children.

Storage: Store at controlled room temperature.

MEDICATED SOLUTION

SOLUTION FOR CLEANSING & FLUSHING OF EARS AND SKIN

FOR DOGS & CATS

ANTIMICROBIAL

CUCUMBER MELON SCENT

Distributed by:
StratfordCare USA
Odessa, FL 33556
877-498-2002
www.stratfordrx.com